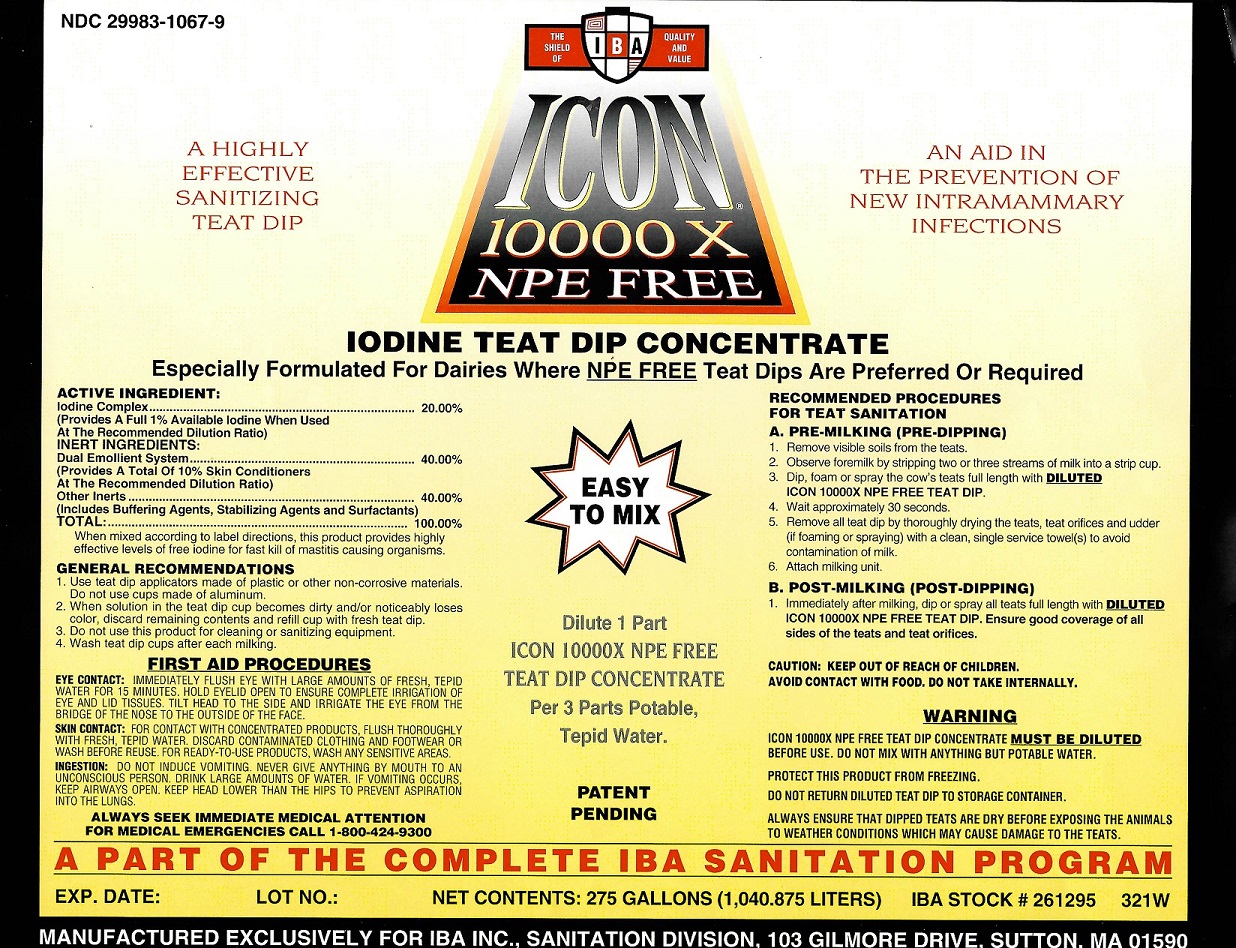 DRUG LABEL: Icon 10000 X NPE Free
NDC: 29983-1067 | Form: LIQUID
Manufacturer: IBA Inc.
Category: animal | Type: OTC ANIMAL DRUG LABEL
Date: 20251202

ACTIVE INGREDIENTS: IODINE 1.00 kg/100 kg

ICON 10000 X NPE Free

ACTIVE INGREDIENT

Iodine Complex.......................................................................20.00%

Provide a full 1% available Iodine when used at the recommended dilution ratio)

Inert Ingredients

Dual emollient system ........................................................... 40.00%

(provides a total of 10% skin conditioners at the recommended dilution ratio)

Other Inerts.......................................................................... 40.00%

(Includes Buffering Agents, Stabilizing Agents and Surfactants)

Total......................................................................................100.00%

When mixed according to label directions, this product provides highly ffective levels of free Iodine for fast kill of mastitis causing organisms.

INDICATIONS AND USAGE

GENERAL RECOMMENDATIONS

1. Use teat dip applicators made of plastic or other non-corrosive materials. Do not use cups made of aluminum.
2. When solution in the teat dip cup becomes dirty and/or noticeably loses color, discard remaining contents and refill cup with fresh teat dip.
3. Do not use this product for cleaning or sanitizing equipment
4. Wash Teat Dip cups after each milking.

RECOMMENDED PROCEDURES FOR TEAT SANITATION
A. PRE-MILKING (PRE-DIPPING)
1. REMOVE VISIBLE SOILS FROM THE TEATS.
2. OBSERVE FOREMILK BY STRIPPING TWO OR THREE STREAMS OF MILK INTO A STRIP CUP.
3. DIP OR SPRAY THE COW'S TEATS FULL LENGTH WITH ICON 1000 X NPE Free TEAT DIP.
4 WAIT APPROXIMATELY 30 SECONDS.
5. REMOVE ALL TEAT DIP BY THOROUGHLY DRYING THE TEATS AND TEAT ORIFICES WITH A CLEAN, SINGLE SERVICE PAPER TOWEL(S).
6. ATTACH MILKING UNIT
B. POST-MILKING (POST DIPPING)
Immediately after milking dip all teats full length with ICON 10000 X NPE Free Teat Dip Ensure good coverage of all sides of the teats and teat orifices.

DILUTE 1 PART ICON 10000 X TEAT DIP PER 3 PARTS POTABLE, TEPID WATER

CAUTION: KEEP OUT OF REACH OF CHILDREN.
AVOID CONTACT WITH FOOD. DO NOT TAKE INTERNALLY.

WARNING

ICON 10000 X NPE Free IODINE TEAT DIP CONCENTRATE MUST BE DILUTED BEFORE USE.
DO NOT MIX WITH ANYTHING BUT POTABLE WATER.
DO NOT RETURN TREAT DIP LEFT IN THE TEAT DIPPER TO STORAGE CONTAINER.
ENSURE THAT DIPPED TEATS ARE DRY BEFORE EXPOSING THE ANIMALS TO WEATHER CONDITIONS WHICH MAY CAUSE DAMAGE TO THE TEATS.
PROTECT THIS PRODUCT FROM FREEZING.

FIRST AID PROCEDURES

EYE CONTACT: IMMEDIATELY FLUSH EYE WITH LARGE AMOUNTS OF FRESH, TEPID WATER FOR 15 MINUTES. HOLD EYELID OPEN TO ENSURE COMPLETE IRRIGATION OF EYE AND LID TISSUES. TILT HEAD TO THE SIDE AND IRRIGATE THE EYE FROM THE BRIDGE OF THE NOSE TO THE OUTSIDE OF THE FACE.
SKIN CONTACT: WASH ANY SENSITIVE AREAS.
INGESTION: DO NOT INDUCE VOMITING. NEVER GIVE ANYTHING BY MOUTH TO AN UNCONSCIOUS PERSON. DRINK LARGE AMOUNTS OF WATER. IF VOMITING OCCURS KEEP AIRWAYS OPEN. KEEP HEAD LOWER THAN THE HIPS TO PREVENT ASPIRATION INTO THE LUNGS.

ALWAYS SEEK IMMEDIATE MEDICAL ATTENTION FOR MEDICAL EMERGENCIES CALL 1-800-424-9300